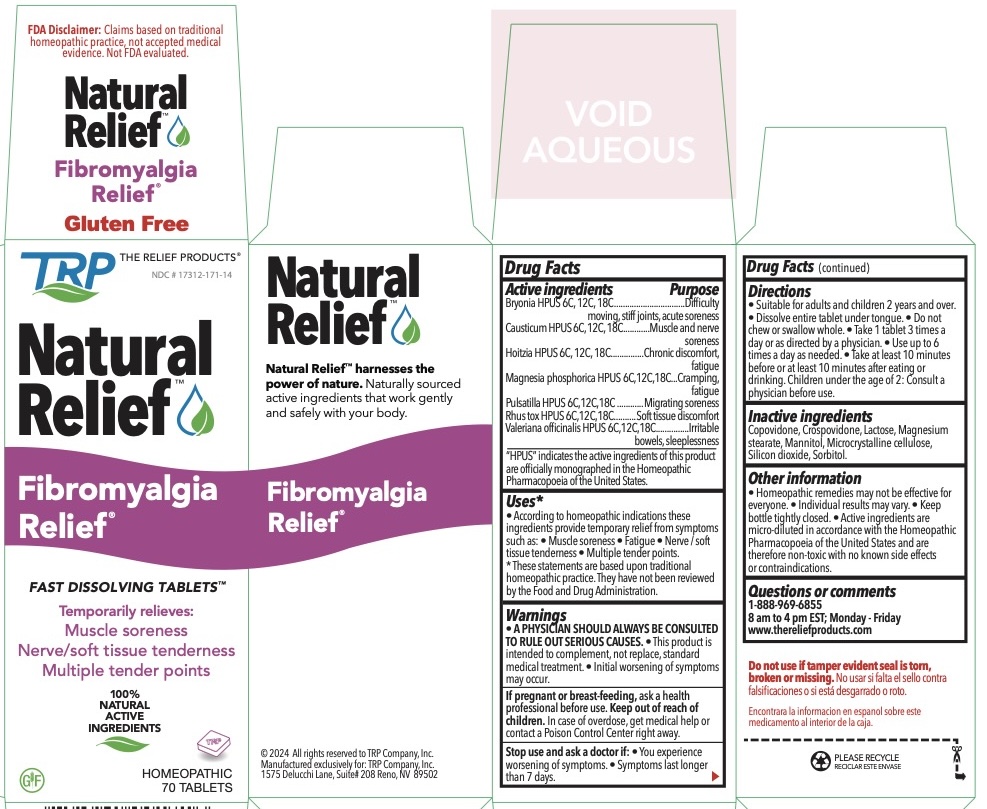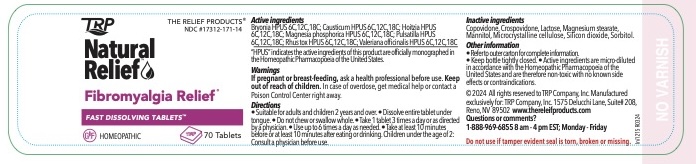 DRUG LABEL: Fibromyalgia Relief
NDC: 17312-171 | Form: TABLET, ORALLY DISINTEGRATING
Manufacturer: TRP Company
Category: homeopathic | Type: HUMAN OTC DRUG LABEL
Date: 20251215

ACTIVE INGREDIENTS: LOESELIA MEXICANA WHOLE 6 [hp_C]/1 1; BRYONIA ALBA ROOT 6 [hp_C]/1 1; CAUSTICUM 6 [hp_C]/1 1; MAGNESIUM PHOSPHATE, DIBASIC TRIHYDRATE 6 [hp_C]/1 1; PULSATILLA VULGARIS 6 [hp_C]/1 1; TOXICODENDRON PUBESCENS LEAF 6 [hp_C]/1 1
INACTIVE INGREDIENTS: MANNITOL; SORBITOL; CROSPOVIDONE; CELLULOSE, MICROCRYSTALLINE; COPOVIDONE; SILICON DIOXIDE; LACTOSE; MAGNESIUM STEARATE

Fibromyalgia Relief® Fast Dissolving Tablets

ACTIVE INGREDIENT

Bryonia HPUS 6C, 12C, 18C
Causticum HPUS 6C, 12C, 18C
Hoitzia HPUS 6C, 12C, 18C
Magnesia phosphorica HPUS 6C,12C,18C
Pulsatilla HPUS 6C,12C,18C
Rhus tox HPUS 6C,12C,18C
Valeriana officinalis HPUS 6C,12C,18C

HPUS indicates the active ingredients are in the Homeopathic Pharmacopoeia of the United States.

PURPOSE

Bryonia HPUS............................Difficulty moving, Stiff joints, acute soreness
Causticum HPUS.......................Muscle and nerve soreness
Hoitzia HPUS.............................Chronic discomfort, fatigue
Magnesia phosphorica HPUS ...Cramping, Fatigue
Pulsatilla HPUS .........................Migrating soreness
Rhus tox HPUS..........................Soft tissue discomfort
Valeriana officinalis HPUS..........Sleeplessness, Irritable bowels

Uses

• According to homeopathic indications these ingredients provide temporary relief from symptoms such as: • Muscle soreness • Fatigue • Nerve / soft tissue tenderness • Multiple tender points; after serious causes have been ruled out by a physician. * These statements are based upon traditional homeopathic practice. They have not been reviewed by the Food and Drug Administration.

PREGNANCY OR BREAST FEEDING

If pregnant or breast-feeding, ask a health professional before use.

Directions

- Suitable for adults and children ages 2 and over. Children under the age of 2: Consult a physician before use.
- Dissolve entire tablet under tongue.
- Do not chew or swallow whole.
- Take 1 tablet 3 times a day or as directed by a physician.
- Use up to 6 times a day as needed.
- Take at least 10 minutes before or at least 10 minutes after eating or drinking. • Homeopathic remedies may not be effective for everyone.
- Individual results may vary. May take up to 60 days to see results.

Other information

• Store at room temperature 15o to 30o C (59o to 86o F). • Keep bottle tightly closed. • Active ingredients are micro-diluted in accordance with the Homeopathic Pharmacopoeia of the United States and are therefore non-toxic with no known side effects or contraindications. • Fibromyalgia Relief® Fast Dissolving TabletsTM are homeopathic dilutions, for details see www.thereliefproducts.com.

Inactive Ingredients

Advantol® 300, Lactose, Magnesium Stearate, Mannitol, Microcrystalline Cellulose.

Do not use if tamper evident seal is torn, broken or missing.

Stop use

Stop use and ask a doctor if:

Symptoms persist for more than 7 days or worsen.

Warnings

• A PHYSICIAN SHOULD ALWAYS BE CONSULTED TO RULE OUT SERIOUS CAUSES.

• This product is intended to complement, not replace, standard medical treatment.

• Initial worsening of symptoms may occur.

Questions or Comments? 888-969-6855 www.thereliefproducts.com